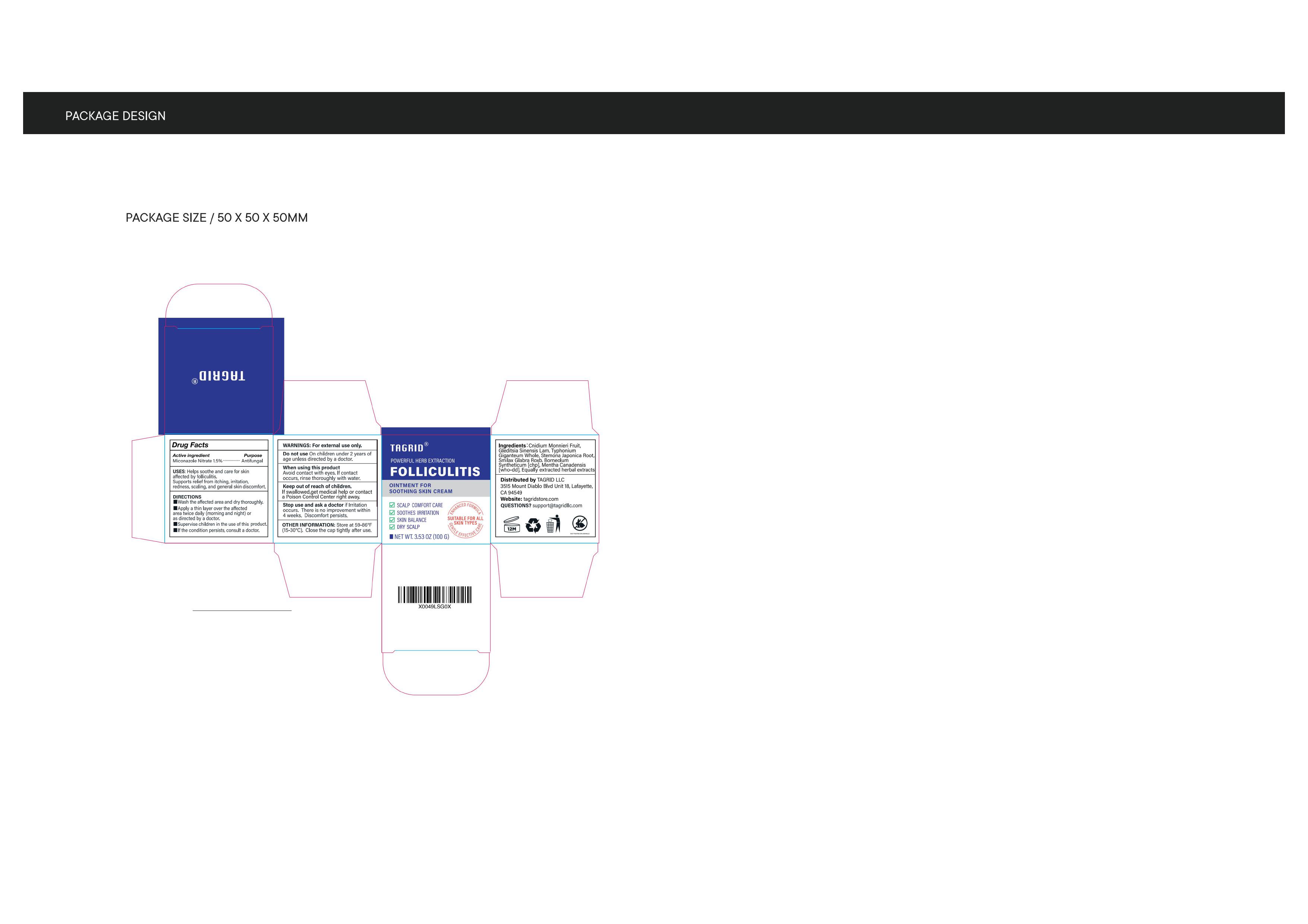 DRUG LABEL: Folliculitis Treatment Cream
NDC: 85384-0004 | Form: CREAM
Manufacturer: TAGRID LLC
Category: otc | Type: HUMAN OTC DRUG LABEL
Date: 20250407

ACTIVE INGREDIENTS: MICONAZOLE NITRATE 15 mg/1 g
INACTIVE INGREDIENTS: CNIDIUM MONNIERI FRUIT; STEMONA JAPONICA ROOT; SMILAX GLABRA TUBER; GLEDITSIA SINENSIS FRUIT; MENTHA CANADENSIS TOP

ACTIVE INGREDIENT

Miconazole Nitrate

PURPOSE

Antifungal

INDICATIONS AND USAGE

Helps soothe and care for skin affected by folliculitis.
Supports relieffrom itching, irritation, redness, scaling, and general skin discomfort.

WARNINGS

For external use only

Do not use On children under 2 years of age unless directed by a doctor.

WHEN USING

Avoid contact with eyes.

If contact occurs, rinse thoroughly with water.

KEEP OUT OF REACH OF CHILDREN

If swallowed,get medical help or contact a Poison Control Center right away.

Stop use and ask a doctor if Irritation occurs. There is no improvement within
4 weeks. Discomfort persists.

OTHER SAFETY INFORMATION

Store at 59-86°F (15-30°C). Close the cap tightly after use.

QUESTIONS

support@tagridllc.com

DOSAGE AND ADMINISTRATION

-Wash the affected area and dry thoroughly.
-Apply a thin layer over the affected area twice daily (morning and night) or
as directed by a doctor.
-Supervise children in the use of this produc
-lf the condition persists, consult a doctor.

INACTIVE INGREDIENT

Ingredients:Cnidium Monnieri Fruit, Gleditsia Sinensis Lam.

Typhonium Giganteum Whole, Stemona Japonica Root,
Smilax Glabra Roxb. Borneolum Syntheticum [chp],

Mentha Canadensis [who-dd], Equally extracted herbal extracts